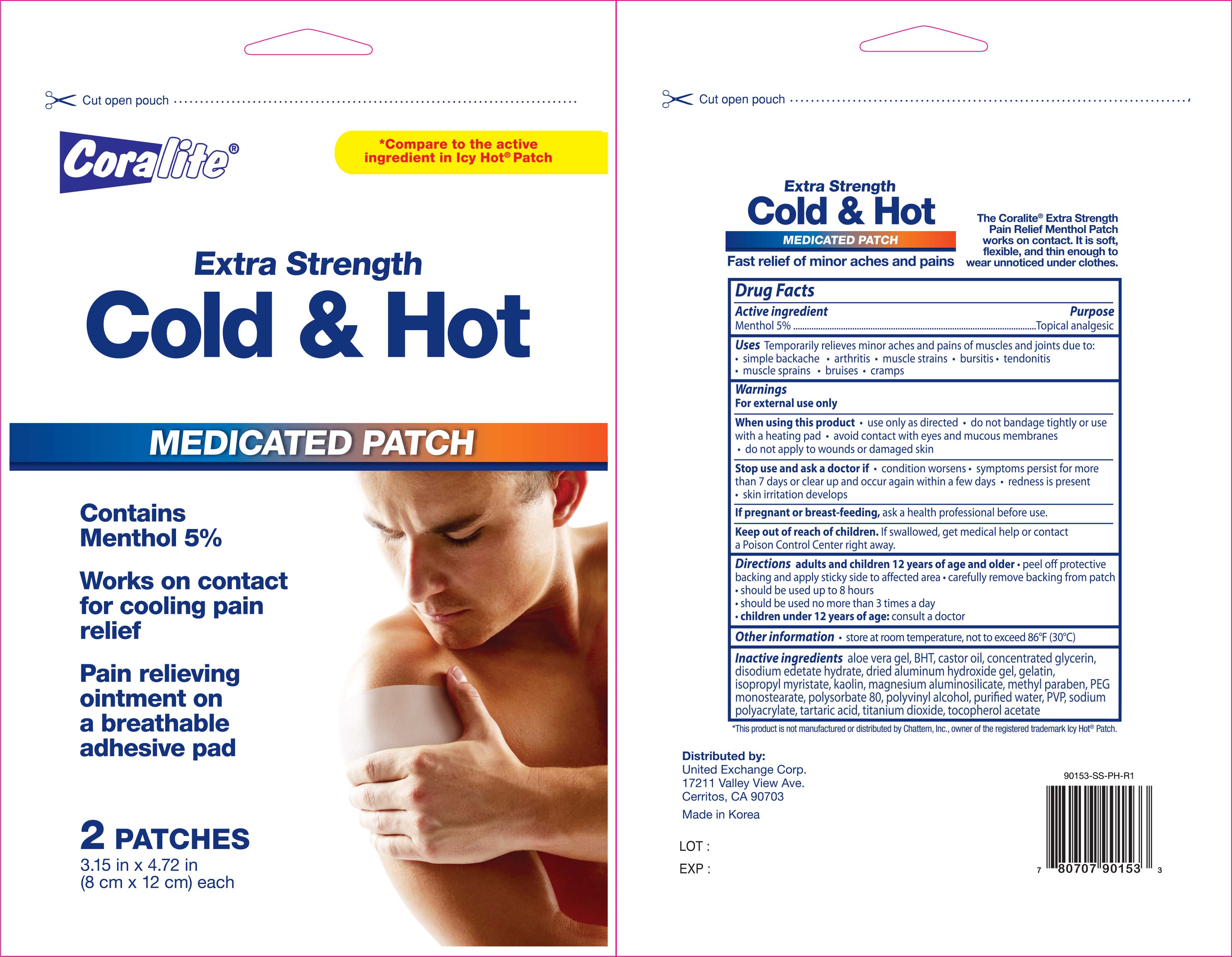 DRUG LABEL: Coralite Cold and Hot
NDC: 65923-153 | Form: PATCH
Manufacturer: United Exchange Corp.
Category: otc | Type: HUMAN OTC DRUG LABEL
Date: 20170720

ACTIVE INGREDIENTS: MENTHOL 5 mg/1 g
INACTIVE INGREDIENTS: ALOE VERA LEAF; BUTYLATED HYDROXYTOLUENE; CASTOR OIL; GLYCERIN; EDETATE DISODIUM; ALUMINUM HYDROXIDE; GELATIN; ISOPROPYL MYRISTATE; KAOLIN; MAGNESIUM ALUMINUM SILICATE; METHYLPARABEN; POLYSORBATE 80; POLYVINYL ALCOHOL, UNSPECIFIED; WATER; SODIUM POLYACRYLATE (8000 MW); TARTARIC ACID; TITANIUM DIOXIDE; ALPHA-TOCOPHEROL ACETATE

Active Ingredient Purpose

Menthol 5%................................................... Topical analgesic

Uses

Temporarily relieves minor aches and pains of muscles and joints due to:

- arthritis
- simple backache
- bursitis
- tendonitis
- muscle sprains
- bruises
- cramps

Warnings

For external use only

When using this product

- use only as directed
- do not bandage tightly or use with a heating pad
- avoid contact with eyes and mucous mebranes
- do not apply to wounds or damaged skin

Stop use and ask a doctor if:

- condition worsens
- symptoms persist for more than 7 days or clear up and occur again within a few days
- redness is present
- skin irritation develops

PREGNANCY OR BREAST FEEDING

If pregnant or breast-feeding, ask a health professional before use

Keep out of reach of children:

- If swallowed, get medical help or contact a Poision Control Center right away

Directions

Adults and children 12 years of age and older

- peel off protective backing and apply sticky side to affected area
- carefully remove backing from patch
- should be used up to 8 hours
- should be used no more than 3 times a day
- children under 12 years of age: consult a doctor

Other Information

- store at room temperature, not to exceed 86°F (30°C)

Inactive ingredients

aloe vera gel, BHT, castor oil, concentrated glycerin, disodium edetate hydrate, dried aluminum hydroxide gel, gelatin, isopropyl myristate, kaolin, magnesium aluminosilicate, methylparaben, PEG, monostearate, polysorbate 80, polyvinyl alcohol, purified water, PVP, sodium polyacrylate, tartaric acid, titanium dioxide, tocopherol acetate

DOSAGE AND ADMINISTRATION

DISTRIBUTED BY:

UNITED EXCHANGE CORP.

17211 VALLEY VIEW AVE.

CERRITOS, CA 90703 USA